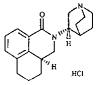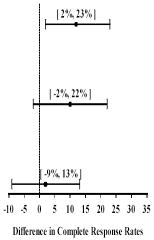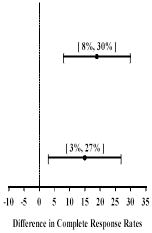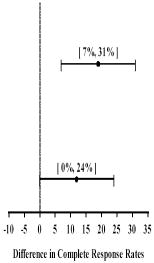 DRUG LABEL: Unknown
Manufacturer: MGI PHARMA
Category: prescription | Type: HUMAN PRESCRIPTION DRUG LABEL WITH HIGHLIGHTS
Date: 20080923

HIGHLIGHTS OF PRESCRIBING INFORMATION

ALOXI® (palonosetron HCl) Injection for Intravenous Use

RECENT MAJOR CHANGES

Indications and Usage, Postoperative and Postdischarge Nausea and Vomiting (1.2) 02/2008

Dosage and Administration, Recommended Dosing (2.1) 02/2008

Warnings and Precautions, QTc Intervals (5.2) - Deletion 02/2008

1 INDICATIONS AND USAGE

ALOXI is a serotonin subtype 3 (5-HT3) receptor antagonist indicated for:

• Moderately emetogenic cancer chemotherapy -- prevention of acute and delayed nausea and vomiting associated with initial and repeat courses (1.1)

• Highly emetogenic cancer chemotherapy -- prevention of acute nausea and vomiting associated with initial and repeat courses (1.1)

• Prevention of postoperative nausea and vomiting (PONV) for up to 24 hours following surgery. Efficacy beyond 24 hours has not been demonstrated (1.2)

2 DOSAGE AND ADMINISTRATION

Chemotherapy Induced Nausea and Vomiting (2.1)

• Adult Dosage: a single 0.25 mg I.V. dose administered over 30 seconds. Dosing should occur approximately 30 minutes before the start of chemotherapy.

Postoperative Nausea and Vomiting (2.1)

• Adult Dosage: a single 0.075 mg I.V. dose administered over 10 seconds immediately before the induction of anesthesia.

3 DOSAGE FORM AND STRENGTHS

0.25 mg/5ml (free base) single-use vial (3)

0.075 mg/1.5ml (free base) single-use vial (3)

4 CONTRAINDICATIONS

ALOXI is contraindicated in patients known to have hypersensitivity to the drug or any of its components (4)

5 WARNINGS AND PRECAUTIONS

• Hypersensitivity reactions may occur in patients who have exhibited hypersensitivity to other selective 5-HT3 receptor antagonists (5.1)

6 ADVERSE REACTIONS

The most common adverse reactions in chemotherapy-induced nausea and vomiting (incidence ≥ 5%) are headache and constipation (6.1)

The most common adverse reactions in postoperative nausea and vomiting (incidence ≥ 2%) are QT prolongation, bradycardia, headache, and constipation.

7 DRUG INTERACTIONS

The potential for clinically significant drug interactions with palonosetron appears to be low (7)

8 USE IN SPECIFIC POPULATIONS

Safety and effectiveness in patients below the age of 18 years have not been established (8.4)

FULL PRESCRIBING INFORMATION

1 INDICATIONS AND USAGE

1.1 Chemotherapy Induced Nausea and Vomiting

ALOXI is indicated for:

• Moderately emetogenic cancer chemotherapy -- prevention of acute and delayed nausea and vomiting associated with initial and repeat courses

• Highly emetogenic cancer chemotherapy -- prevention of acute nausea and vomiting associated with initial and repeat courses

1.2 Postoperative Nausea and Vomiting

ALOXI is indicated for:

• Prevention of postoperative nausea and vomiting (PONV) for up to 24 hours following surgery. Efficacy beyond 24 hours has not been demonstrated.

As with other antiemetics, routine prophylaxis is not recommended in patients in whom there is little expectation that nausea and/or vomiting will occur postoperatively. In patients where nausea and vomiting must be avoided during the postoperative period, ALOXI is recommended even where the incidence of postoperative nausea and/or vomiting is low.

2 DOSAGE AND ADMINISTRATION

2.1 Recommended Dosing

Chemotherapy Induced Nausea and Vomiting

Dosage for Adults - a single 0.25 mg I.V. dose administered over 30 seconds. Dosing should occur approximately 30 minutes before the start of chemotherapy.

Postoperative Nausea and Vomiting

Dosage for Adults - a single 0.075 mg I.V. dose administered over 10 seconds immediately before induction of anesthesia.

2.2 Instructions for I.V. Administration

ALOXI is supplied ready for intravenous injection. ALOXI should not be mixed with other drugs. Flush the infusion line with normal saline before and after administration of ALOXI.

Parenteral drug products should be inspected visually for particulate matter and discoloration before administration, whenever solution and container permit.

3 DOSAGE FORM AND STRENGTHS

Aloxi is supplied as a single-use sterile, clear, colorless solution in glass vials that provide:

• 0.25 mg (free base) per 5 mL

• 0.075 mg (free base) per 1.5 mL

4 CONTRAINDICATIONS

ALOXI is contraindicated in patients known to have hypersensitivity to the drug or any of its components. [see Adverse Reactions (6.2)]

5 WARNINGS AND PRECAUTIONS

5.1 Hypersensitivity

Hypersensitivity reactions may occur in patients who have exhibited hypersensitivity to other 5-HT3 receptor antagonists.

6 ADVERSE REACTIONS

Because clinical trials are conducted under widely varying conditions, adverse reaction rates observed in the clinical trials of a drug cannot be directly compared to rates in the clinical trials of another drug and may not reflect the rates observed in practice.

6.1 Chemotherapy-Induced Nausea And Vomiting

In clinical trials for the prevention of nausea and vomiting induced by moderately or highly emetogenic chemotherapy, 1374 adult patients received palonosetron. Adverse reactions were similar in frequency and severity with Aloxi and ondansetron or dolasetron. Following is a listing of all adverse reactions reported by ≥ 2% of patients in these trials (Table 1).

Table 1: Adverse Reactions from Chemotherapy-Induced Nausea and Vomiting Studies ≥ 2% in any Treatment Group
Event | Aloxi 0.25 mg (N=633) | Ondansetron 32 mg I.V. (N=410) | Dolasetron 100 mg I.V. (N=194)
Headache | 60 (9%) | 34 (8%) | 32 (16%)
Constipation | 29 (5%) | 8 (2%) | 12 (6%)
Diarrhea | 8 (1%) | 7 (2%) | 4 (2%)
Dizziness | 8 (1%) | 9 (2%) | 4 (2%)
Fatigue | 3 (< 1%) | 4 (1%) | 4 (2%)
Abdominal Pain | 1 (< 1%) | 2 (< 1%) | 3 (2%)
Insomnia | 1 (< 1%) | 3 (1%) | 3 (2%)

In other studies, 2 subjects experienced severe constipation following a single palonosetron dose of approximately 0.75 mg, three times the recommended dose. One patient received a 10 mcg/kg oral dose in a post-operative nausea and vomiting study and one healthy subject received a 0.75 mg I.V. dose in a pharmacokinetic study.

In clinical trials, the following infrequently reported adverse reactions, assessed by investigators as treatment-related or causality unknown, occurred following administration of Aloxi to adult patients receiving concomitant cancer chemotherapy:

Cardiovascular: 1%: non-sustained tachycardia, bradycardia, hypotension, < 1%: hypertension, myocardial ischemia, extrasystoles, sinus tachycardia, sinus arrhythmia, supraventricular extrasystoles and QT prolongation. In many cases, the relationship to Aloxi was unclear.

Dermatological: < 1%: allergic dermatitis, rash.

Hearing and Vision: < 1%: motion sickness, tinnitus, eye irritation and amblyopia.

Gastrointestinal System: 1%: diarrhea, < 1%: dyspepsia, abdominal pain, dry mouth, hiccups and flatulence.

General: 1%: weakness, < 1%: fatigue, fever, hot flash, flu-like syndrome.

Liver: < 1%: transient, asymptomatic increases in AST and/or ALT and bilirubin. These changes occurred predominantly in patients receiving highly emetogenic chemotherapy.

Metabolic: 1%: hyperkalemia, < 1%: electrolyte fluctuations, hyperglycemia, metabolic acidosis, glycosuria, appetite decrease, anorexia.

Musculoskeletal: < 1%: arthralgia.

Nervous System: 1%: dizziness, < 1%: somnolence, insomnia, hypersomnia, paresthesia.

Psychiatric: 1%: anxiety, < 1%: euphoric mood.

Urinary System: < 1%: urinary retention.

Vascular: < 1%: vein discoloration, vein distention.

6.2 Postoperative Nausea And Vomiting

The adverse reactions cited in Table 2 were reported in ≥ 2% of adults receiving I.V. Aloxi 0.075 mg immediately before induction of anesthesia in one phase 2 and two phase 3 randomized placebo-controlled trials. Rates of events between palonosetron and placebo groups were indistinguishable. Some events are known to be associated with, or may be exacerbated by concomitant perioperative and intraoperative medications administered in this surgical population. Please refer to Section 12.2, thorough QT/QTc study results, for definitive data demonstrating the lack of palonosetron effect on QT/QTc.

Table 2: Adverse Reactions from Postoperative Nausea and Vomiting Studies ≥ 2% in any Treatment Group
Event | Aloxi 0.075 mg (N=336) | Placebo (N=369)
Electrocardiogram QT prolongation | 16 (5%) | 11 (3%)
Bradycardia | 13 (4%) | 16 (4%)
Headache | 11 (3%) | 14 (4%)
Constipation | 8 (2%) | 11 (3%)

In these clinical trials, the following infrequently reported adverse reactions, assessed by investigators as treatment-related or causality unknown, occurred following administration of ALOXI to adult patients receiving concomitant perioperative and intraoperative medications including those associated with anesthesia:

Cardiovascular: 1%: electrocardiogram QTc prolongation, sinus bradycardia, tachycardia; < 1%: blood pressure decreased, hypotension, hypertension, arrhythmia, ventricular extrasystoles, generalized edema; ECG T wave amplitude decreased, platelet count decreased. The frequency of these adverse effects did not appear to be different from placebo.

Dermatological: 1%: pruritus.

Gastrointestinal System: 1%: flatulence, < 1%: dry mouth, upper abdominal pain, salivary hypersecretion, dyspepsia, diarrhea, intestinal hypomotility, anorexia.

General: < 1%: chills.

Liver: 1%: increases in AST and/or ALT< 1%: hepatic enzyme increased

Metabolic: < 1%: hypokalemia, anorexia.

Nervous System: < 1%: dizziness.

Respiratory: < 1%: hypoventilation, laryngospasm.

Urinary System: 1%: urinary retention.

6.3 Postmarketing Experience

The following adverse reactions have been identified during postapproval use of ALOXI. Because these reactions are reported voluntarily from a population of uncertain size, it is not always possible to reliably estimate their frequency or establish a causal relationship to drug exposure.

Very rare cases (<1/10,000) of hypersensitivity reactions and injection site reactions (burning, induration, discomfort and pain) were reported from postmarketing experience of ALOXI 0.25 mg in the prevention of chemotherapy-induced nausea and vomiting.

7 DRUG INTERACTIONS

Palonosetron is eliminated from the body through both renal excretion and metabolic pathways with the latter mediated via multiple CYP enzymes. Further in vitro studies indicated that palonosetron is not an inhibitor of CYP1A2, CYP2A6, CYP2B6, CYP2C9, CYP2D6, CYP2E1 and CYP3A4/5 (CYP2C19 was not investigated) nor does it induce the activity of CYP1A2, CYP2D6, or CYP3A4/5. Therefore, the potential for clinically significant drug interactions with palonosetron appears to be low.

Coadministration of 0.25 mg I.V. palonosetron and 20 mg I.V. dexamethasone in healthy subjects revealed no pharmacokinetic drug-interactions between palonosetron and dexamethasone.

In an interaction study in healthy subjects where palonosetron 0.25 mg (I.V. bolus) was administered on day 1 and oral aprepitant for 3 days (125 mg/80 mg/80 mg), the pharmacokinetics of palonosetron were not significantly altered (AUC: no change, Cmax: 15% increase).

A study in healthy volunteers involving single-dose I.V. palonosetron (0.75 mg) and steady state oral metoclopramide (10 mg four times daily) demonstrated no significant pharmacokinetic interaction.

In controlled clinical trials, ALOXI injection has been safely administered with corticosteroids, analgesics, antiemetics/antinauseants, antispasmodics and anticholinergic agents.

Palonosetron did not inhibit the antitumor activity of the five chemotherapeutic agents tested (cisplatin, cyclophosphamide, cytarabine, doxorubicin and mitomycin C) in murine tumor models.

8 USE IN SPECIFIC POPULATIONS

8.1 Pregnancy

Teratogenic Effects: Category B

Teratology studies have been performed in rats at oral doses up to 60 mg/kg/day (1894 times the recommended human intravenous dose based on body surface area) and rabbits at oral doses up to 60 mg/kg/day (3789 times the recommended human intravenous dose based on body surface area) and have revealed no evidence of impaired fertility or harm to the fetus due to palonosetron. There are, however, no adequate and well-controlled studies in pregnant women. Because animal reproduction studies are not always predictive of human response, palonosetron should be used during pregnancy only if clearly needed.

8.2 Labor and Delivery

Palonosetron has not been administered to patients undergoing labor and delivery, so its effects on the mother or child are unknown.

8.3 Nursing Mothers

It is not known whether palonosetron is excreted in human milk. Because many drugs are excreted in human milk and because of the potential for serious adverse reactions in nursing infants and the potential for tumorigenicity shown for palonosetron in the rat carcinogenicity study, a decision should be made whether to discontinue nursing or to discontinue the drug, taking into account the importance of the drug to the mother.

8.4 Pediatric Use

Safety and effectiveness in patients below the age of 18 years have not been established.

8.5 Geriatric Use

Population pharmacokinetics analysis did not reveal any differences in palonosetron pharmacokinetics between cancer patients ≥ 65 years of age and younger patients (18 to 64 years). Of the 1374 adult cancer patients in clinical studies of palonosetron, 316 (23%) were ≥ 65 years old, while 71 (5%) were ≥ 75 years old. No overall differences in safety or effectiveness were observed between these subjects and the younger subjects, but greater sensitivity in some older individuals cannot be ruled out. No dose adjustment or special monitoring are required for geriatric patients.

Of the 1520 adult patients in Aloxi PONV and PDNV clinical studies, 73 (5%) were ≥ 65 years old. No overall differences in safety were observed between older and younger subjects in these studies, though the possibility of heightened sensitivity in some older individuals cannot be excluded. No differences in efficacy were observed in geriatric patients for the CINV indication and none are expected for geriatric PONV patients. However, Aloxi efficacy in geriatric patients has not been adequately evaluated.

8.6 Renal Impairment

Mild to moderate renal impairment does not significantly affect palonosetron pharmacokinetic parameters. Total systemic exposure increased by approximately 28% in severe renal impairment relative to healthy subjects. Dosage adjustment is not necessary in patients with any degree of renal impairment.

8.7 Hepatic Impairment

Hepatic impairment does not significantly affect total body clearance of palonosetron compared to the healthy subjects. Dosage adjustment is not necessary in patients with any degree of hepatic impairment.

8.8 Race

Intravenous palonosetron pharmacokinetics was characterized in twenty-four healthy Japanese subjects over the dose range of 3 - 90 mcg/kg. Total body clearance was 25% higher in Japanese subjects compared to Whites, however, no dose adjustment is required. The pharmacokinetics of palonosetron in Blacks has not been adequately characterized.

10 OVERDOSAGE

There is no known antidote to ALOXI. Overdose should be managed with supportive care.

Fifty adult cancer patients were administered palonosetron at a dose of 90 mcg/kg (equivalent to 6 mg fixed dose) as part of a dose ranging study. This is approximately 25 times the recommended dose of 0.25 mg. This dose group had a similar incidence of adverse events compared to the other dose groups and no dose response effects were observed.

Dialysis studies have not been performed, however, due to the large volume of distribution, dialysis is unlikely to be an effective treatment for palonosetron overdose. A single intravenous dose of palonosetron at 30 mg/kg (947 and 474 times the human dose for rats and mice, respectively, based on body surface area) was lethal to rats and mice. The major signs of toxicity were convulsions, gasping, pallor, cyanosis and collapse.

11 DESCRIPTION

ALOXI (palonosetron hydrochloride) is an antiemetic and antinauseant agent. It is a serotonin subtype 3 (5-HT3) receptor antagonist with a strong binding affinity for this receptor. Chemically, palonosetron hydrochloride is: (3aS)-2-[(S)-1-Azabicyclo [2.2.2]oct-3-yl]-2,3,3a,4,5,6-hexahydro-1-oxo-1Hbenz[de]isoquinoline hydrochloride. The empirical formula is C19H24N2O.HCl, with a molecular weight of 332.87. Palonosetron hydrochloride exists as a single isomer and has the following structural formula:

Palonosetron hydrochloride is a white to off-white crystalline powder. It is freely soluble in water, soluble in propylene glycol, and slightly soluble in ethanol and 2-propanol.

ALOXI injection is a sterile, clear, colorless, non pyrogenic, isotonic, buffered solution for intravenous administration. ALOXI injection is available as 5-mL single use vial or 1.5-mL single use vial. Each 5-mL vial contains 0.25 mg palonosetron base as 0.28 mg palonosetron hydrochloride, 207.5 mg mannitol, disodium edetate and citrate buffer in water for intravenous administration.

Each 1.5-mL vial contains 0.075 mg palonosetron base as 0.084 mg palonosetron hydrochloride, 83 mg mannitol, disodium edetate and citrate buffer in water for intravenous administration.

The pH of the solution in the 5-mL and 1.5-mL vials is 4.5 to 5.5.

12 CLINICAL PHARMACOLOGY

12.1 Mechanism of Action

Palonosetron is a 5-HT3 receptor antagonist with a strong binding affinity for this receptor and little or no affinity for other receptors.

Cancer chemotherapy may be associated with a high incidence of nausea and vomiting, particularly when certain agents, such as cisplatin, are used. 5-HT3 receptors are located on the nerve terminals of the vagus in the periphery and centrally in the chemoreceptor trigger zone of the area postrema. It is thought that chemotherapeutic agents produce nausea and vomiting by releasing serotonin from the enterochromaffin cells of the small intestine and that the released serotonin then activates 5-HT3 receptors located on vagal afferents to initiate the vomiting reflex

Postoperative nausea and vomiting is influenced by multiple patient, surgical and anesthesia related factors and is triggered by release of 5-HT in a cascade of neuronal events involving both the central nervous system and the gastrointestinal tract. The 5-HT3 receptor has been demonstrated to selectively participate in the emetic response.

12.2 Pharmacodynamics

The effect of palonosetron on blood pressure, heart rate, and ECG parameters including QTc were comparable to ondansetron and dolasetron in CINV clinical trials. In PONV clinical trials the effect of palonosetron on the QTc interval was no different from placebo. In non-clinical studies palonosetron possesses the ability to block ion channels involved in ventricular de- and re-polarization and to prolong action potential duration.

The effect of palonosetron on QTc interval was evaluated in a double blind, randomized, parallel, placebo and positive (moxifloxacin) controlled trial in adult men and women. The objective was to evaluate the ECG effects of I.V. administered palonosetron at single doses of 0.25, 0.75 or 2.25 mg in 221 healthy subjects. The study demonstrated no significant effect on any ECG interval including QTc duration (cardiac repolarization) at doses up to 2.25 mg.

12.3 Pharmacokinetics

After intravenous dosing of palonosetron in healthy subjects and cancer patients, an initial decline in plasma concentrations is followed by a slow elimination from the body. Mean maximum plasma concentration (Cmax) and area under the concentration-time curve (AUC0-∞) are generally dose-proportional over the dose range of 0.3-90 mcg/kg in healthy subjects and in cancer patients. Following single I.V. dose of palonosetron at 3 mcg/kg (or 0.21 mg/70 kg) to six cancer patients, mean (±SD) maximum plasma concentration was estimated to be 5.6 ± 5.5 ng/mL and mean AUC was 35.8 ± 20.9 ng•hr/mL.

Following I.V. administration of palonosetron 0.25 mg once every other day for 3 doses in 11 cancer patients, the mean increase in plasma palonosetron concentration from Day 1 to Day 5 was 42±34%. Following I.V. administration of palonosetron 0.25 mg once daily for 3 days in 12 healthy subjects, the mean (±SD) increase in plasma palonosetron concentration from Day 1 to Day 3 was 110±45%.

After intravenous dosing of palonosetron in patients undergoing surgery (abdominal surgery or vaginal hysterectomy), the pharmacokinetic characteristics of palonosetron were similar to those observed in cancer patients.

Distribution

Palonosetron has a volume of distribution of approximately 8.3 ± 2.5 L/kg. Approximately 62% of palonosetron is bound to plasma proteins.

Metabolism

Palonosetron is eliminated by multiple routes with approximately 50% metabolized to form two primary metabolites: N-oxide-palonosetron and 6-S-hydroxy-palonosetron. These metabolites each have less than 1% of the 5-HT3 receptor antagonist activity of palonosetron. In vitro metabolism studies have suggested that CYP2D6 and to a lesser extent, CYP3A4 and CYP1A2 are involved in the metabolism of palonosetron. However, clinical pharmacokinetic parameters are not significantly different between poor and extensive metabolizers of CYP2D6 substrates.

Elimination

After a single intravenous dose of 10 mcg/kg [^14C]-palonosetron, approximately 80% of the dose was recovered within 144 hours in the urine with palonosetron representing approximately 40% of the administered dose. In healthy subjects, the total body clearance of palonosetron was 160 ± 35 mL/h/kg and renal clearance was 66.5± 18.2 mL/h/kg. Mean terminal elimination half-life is approximately 40 hours.

Special Populations

[See USE IN SPECIFIC POPULATIONS (8.5 - 8.8)].

13 NONCLINICAL TOXICOLOGY

13.1 Carcinogenesis, Mutagenesis, Impairment of Fertility

In a 104-week carcinogenicity study in CD-1 mice, animals were treated with oral doses of palonosetron at 10, 30 and 60 mg/kg/day. Treatment with palonosetron was not tumorigenic. The highest tested dose produced a systemic exposure to palonosetron (Plasma AUC) of about 150 to 289 times the human exposure (AUC= 29.8 ng•h/mL) at the recommended intravenous dose of 0.25 mg. In a 104-week carcinogenicity study in Sprague-Dawley rats, male and female rats were treated with oral doses of 15, 30 and 60 mg/kg/day and 15, 45 and 90 mg/kg/day, respectively. The highest doses produced a systemic exposure to palonosetron (Plasma AUC) of 137 and 308 times the human exposure at the recommended dose. Treatment with palonosetron produced increased incidences of adrenal benign pheochromocytoma and combined benign and malignant pheochromocytoma, increased incidences of pancreatic Islet cell adenoma and combined adenoma and carcinoma and pituitary adenoma in male rats. In female rats, it produced hepatocellular adenoma and carcinoma and increased the incidences of thyroid C-cell adenoma and combined adenoma and carcinoma.

Palonosetron was not genotoxic in the Ames test, the Chinese hamster ovarian cell (CHO/HGPRT) forward mutation test, the ex vivo hepatocyte unscheduled DNA synthesis (UDS) test or the mouse micronucleus test. It was, however, positive for clastogenic effects in the Chinese hamster ovarian (CHO) cell chromosomal aberration test.

Palonosetron at oral doses up to 60 mg/kg/day (about 1894 times the recommended human intravenous dose based on body surface area) was found to have no effect on fertility and reproductive performance of male and female rats.

14 CLINICAL STUDIES

14.1 Chemotherapy-Induced Nausea And Vomiting

Efficacy of single-dose palonosetron injection in preventing acute and delayed nausea and vomiting induced by both moderately and highly emetogenic chemotherapy was studied in three Phase 3 trials and one Phase 2 trial. In these double-blind studies, complete response rates (no emetic episodes and no rescue medication) and other efficacy parameters were assessed through at least 120 hours after administration of chemotherapy. The safety and efficacy of palonosetron in repeated courses of chemotherapy was also assessed.

Moderately Emetogenic Chemotherapy

Two Phase 3, double-blind trials involving 1132 patients compared single-dose I.V. Aloxi with either single-dose I.V. ondansetron (study 1) or dolasetron (study 2) given 30 minutes prior to moderately emetogenic chemotherapy including carboplatin, cisplatin ≤ 50 mg/m^2, cyclophosphamide < 1500 mg/m^2, doxorubicin > 25 mg/m^2, epirubicin, irinotecan, and methotrexate > 250 mg/m^2. Concomitant corticosteroids were not administered prophylactically in study 1 and were only used by 4-6% of patients in study 2. The majority of patients in these studies were women (77%), White (65%) and naïve to previous chemotherapy (54%). The mean age was 55 years.

Highly Emetogenic Chemotherapy

A Phase 2, double-blind, dose-ranging study evaluated the efficacy of single-dose I.V. palonosetron from 0.3 to 90 mcg/kg (equivalent to < 0.1 mg to 6 mg fixed dose) in 161 chemotherapy-naïve adult cancer patients receiving highly-emetogenic chemotherapy (either cisplatin ≥ 70 mg/m^2 or cyclophosphamide > 1100 mg/m^2). Concomitant corticosteroids were not administered prophylactically. Analysis of data from this trial indicates that 0.25 mg is the lowest effective dose in preventing acute nausea and vomiting induced by highly emetogenic chemotherapy.

A Phase 3, double-blind trial involving 667 patients compared single-dose I.V. Aloxi with single-dose I.V. ondansetron (study 3) given 30 minutes prior to highly emetogenic chemotherapy including cisplatin ≥ 60 mg/m^2, cyclophosphamide > 1500 mg/m^2, and dacarbazine. Corticosteroids were co-administered prophylactically before chemotherapy in 67% of patients. Of the 667 patients, 51% were women, 60% White, and 59% naïve to previous chemotherapy. The mean age was 52 years.

Efficacy Results

The antiemetic activity of Aloxi was evaluated during the acute phase (0-24 hours) [Table 3], delayed phase (24-120 hours) [Table 4], and overall phase (0-120 hours) [Table 5] post-chemotherapy in Phase 3 trials.

Table 3: Prevention of Acute Nausea and Vomiting (0-24 hours): Complete Response Rates
Chemotherapy | Study | Treatment Group | N [Intent-to-treat cohort] | % with Complete Response | p-value [2-sided Fisher's exact test. Significance level at α=0.025.] | 97.5% Confidence Interval ALOXI minus Comparator [These studies were designed to show non-inferiority. A lower bound greater than -15% demonstrates non-inferiority between ALOXI and comparator.]
Moderately Emetogenic | 1 | ALOXI 0.25 mg | 189 | 81 | 0.009
Moderately Emetogenic | 1 | Ondansetron 32 mg I.V. | 185 | 69 | 0.009
Moderately Emetogenic | 2 | ALOXI 0.25 mg | 189 | 63 | NS
Moderately Emetogenic | 2 | Dolasetron 100 mg I.V. | 191 | 53 | NS
Highly Emetogenic | 3 | ALOXI 0.25 mg | 223 | 59 | NS
Highly Emetogenic | 3 | Ondansetron 32 mg I.V. | 221 | 57 | NS

These studies show that ALOXI was effective in the prevention of acute nausea and vomiting associated with initial and repeat courses of moderately and highly emetogenic cancer chemotherapy. In study 3, efficacy was greater when prophylactic corticosteroids were administered concomitantly. Clinical superiority over other 5-HT3 receptor antagonists has not been adequately demonstrated in the acute phase.

Table 4: Prevention of Delayed Nausea and Vomiting (24-120 hours): Complete Response Rates
Chemotherapy | Study | Treatment Group | N [Intent-to-treat cohort] | % with Complete Response | p-value [2-sided Fisher's exact test. Significance level at α=0.025.] | 97.5% Confidence Interval ALOXI minus Comparator [These studies were designed to show non-inferiority. A lower bound greater than -15% demonstrates non-inferiority between ALOXI and comparator.]
Moderately Emetogenic | 1 | ALOXI 0.25 mg | 189 | 74 | <0.001
Moderately Emetogenic | 1 | Ondansetron 32 mg I.V. | 185 | 55 | <0.001
Moderately Emetogenic | 2 | ALOXI 0.25 mg | 189 | 54 | 0.004
Moderately Emetogenic | 2 | Dolasetron 100 mg I.V. | 191 | 39 | 0.004

These studies show that ALOXI was effective in the prevention of delayed nausea and vomiting associated with initial and repeat courses of moderately emetogenic chemotherapy.

Table 5: Prevention of Overall Nausea and Vomiting (0-120 hours): Complete Response Rates
Chemotherapy | Study | Treatment Group | N [Intent-to-treat cohort] | % with Complete Response | p-value [2-sided Fisher's exact test. Significance level at α=0.025.] | 97.5% Confidence Interval ALOXI minus Comparator [These studies were designed to show non-inferiority. A lower bound greater than -15% demonstrates non-inferiority between ALOXI and comparator.]
Moderately Emetogenic | 1 | ALOXI 0.25 mg | 189 | 69 | <0.001
Moderately Emetogenic | 1 | Ondansetron 32 mg I.V. | 185 | 50 | <0.001
Moderately Emetogenic | 2 | ALOXI 0.25 mg | 189 | 46 | 0.021
Moderately Emetogenic | 2 | Dolasetron 100 mg I.V. | 191 | 34 | 0.021

These studies show that ALOXI was effective in the prevention of nausea and vomiting throughout the 120 hours (5 days) following initial and repeat courses of moderately emetogenic cancer chemotherapy.

14.2 Postoperative And Post Discharge Nausea And Vomiting

In one multicenter, randomized, stratified, double-blind, parallel-group, phase 3 clinical study (Study 1), palonosetron was compared with placebo for the prevention of PONV in 546 patients undergoing abdominal and gynecological surgery. All patients received general anesthesia. Study 1 was a pivotal study conducted predominantly in the US in the out-patient setting for patients undergoing elective gynecologic or abdominal laparoscopic surgery and stratified at randomization for the following risk factors: gender, non-smoking status, history of post operative nausea and vomiting and/or motion sickness.

In Study 1 patients were randomized to receive palonosetron 0.025 mg, 0.050 mg or 0.075 mg or placebo, each given intravenously immediately prior to induction of anesthesia. The antiemetic activity of palonosetron was evaluated during the 0 to 72 hour time period after surgery.

Of the 138 patients treated with 0.075 mg palonosetron in Study 1 and evaluated for efficacy, 96% were women; 66% had a history of PONV or motion sickness; 85% were non-smokers. As for race, 63% were White, 20% were Black, 15% were Hispanic, and 1% were Asian. The age of patients ranged from 21 to 74 years, with a mean age of 37.9 years. Three patients were greater than 65 years of age.

Co-primary efficacy measures were Complete Response (CR) defined as no emetic episode and no use of rescue medication in the 0-24 and in the 24-72 hours postoperatively.

Secondary efficacy endpoints included:

- Complete Response (CR) 0-48 and 0-72 hours
- Complete Control (CC) defined as CR and no more than mild nausea
- Severity of nausea (none, mild, moderate, severe)

The primary hypothesis in Study 1 was that at least one of the three palonosetron doses were superior to placebo.

Results for Complete Response in Study 1 for 0.075 mg palonosetron versus placebo are described in the following table.

Table 6: Prevention of Postoperative Nausea and Vomiting: Complete Response (CR), Study 1, Palonosetron 0.075 mg Vs Placebo
Treatment | n/N (%) | Palonosetron Vs Placebo
Treatment | n/N (%) | Δ | p-value*
Co-primary Endpoints
CR 0-24 hours
Palonosetron | 59/138 (42.8%) | 16.8% | 0.004
Placebo | 35/135 (25.9%)
CR 24-72 hours
Palonosetron | 67/138 (48.6%) | 7.8% | 0.188
Placebo | 55/135 (40.7%)
* To reach statistical significance for each co-primary endpoint, the required significance limit for the lowest p-value was p<0.017.
Δ Difference (%): palonosetron 0.075 mg minus placebo

Palonosetron 0.075 mg reduced the severity of nausea compared to placebo. Analyses of other secondary endpoints indicate that palonosetron 0.075 mg was numerically better than placebo, however, statistical significance was not formally demonstrated.

A phase 2 randomized, double-blind, multicenter, placebo-controlled, dose ranging study was performed to evaluate I.V. palonosetron for the prevention of post-operative nausea and vomiting following abdominal or vaginal hysterectomy. Five I.V. palonosetron doses (0.1, 0.3, 1.0, 3.0 and 30 μg/kg) were evaluated in a total of 381 intent-to-treat patients. The primary efficacy measure was the proportion of patients with CR in the first 24 hours after recovery from surgery. The lowest effective dose was palonosetron 1 μg/kg (approximately 0.075 mg) which had a CR rate of 44% versus 19% for placebo, p=0.004. Palonosetron 1 μg/kg also significantly reduced the severity of nausea versus placebo, p=0.009.

16 HOW SUPPLIED/STORAGE AND HANDLING

NDC # 58063-797-25, ALOXI Injection 0.25 mg/5 mL (free base) single-use vial individually packaged in a carton.

NDC # 58063-797-37, ALOXI Injection 0.075 mg/1.5 mL (free base) single-use vial packaged in a carton containing 5 vials.

Storage

• Store at controlled temperature of 20-25°C (68°F-77°F). Excursions permitted to 15-30°C (59-86°F).

• Protect from freezing.

• Protect from light.

17 PATIENT COUNSELING INFORMATION

[See FDA-Approved Patient Labeling (17.2)]

17.1 Instructions for Patients

Patients should be advised to report to their physician all of their medical conditions, any pain, redness, or swelling in and around the infusion site [see Adverse Reactions 6.2].

Patients should be instructed to read the patient insert.

17.2 FDA-Approved Patient Labeling

Patient Information

ALOXI®(Ah-lock-see)

Palonosetron HCI injection

Read the Patient Information that comes with ALOXI before your treatment with ALOXI and each time you get ALOXI. There may be new information. This information does not take the place of talking with your doctor about your medical condition or your treatment. If you have questions about ALOXI, ask your doctor or pharmacist.

What is ALOXI?

ALOXI is a medicine called an "antiemetic." ALOXI is used in adults to help prevent the nausea and vomiting that happens:

- right away with certain anti-cancer medicines (chemotherapy)
- or later with certain anti-cancer medicines
- right away after recovery from anesthesia after surgery

What is ALOXI used for?

ALOXI is used to prevent nausea and vomiting that may happen:

- soon after taking certain anti-cancer medicines
- later after taking certain anti-cancer medicines
- soon after recovery from anesthesia after surgery

Who should not take ALOXI?

Do not take ALOXI if you are allergic to any of the ingredients in ALOXI. The active ingredient is palonosetron hydrochloride. See the end of this leaflet for a complete list of ingredients in ALOXI.

ALOXI has not been studied in children under 18 years of age.

What should I tell my doctor before using ALOXI?

Tell your doctor about all of your medical conditions, including if you:

- are pregnant. It is not known if ALOXI may harm your unborn baby. You and your doctor should decide if ALOXI is right for you.
- are breastfeeding. It is not known if ALOXI passes into your milk and if it can harm your baby. You should choose to either take ALOXI or breastfeed, but not both.

Tell your doctor about all of the medicines you take including prescription and nonprescription medicines, vitamins and herbal supplements.

How should I use ALOXI?

ALOXI is given in your vein by I.V. (intravenous) injection. It is only given to you by a healthcare provider in a hospital or clinic. ALOXI is usually injected into your vein about 30 minutes before you get your anti-cancer medicine (chemotherapy) or immediately before anesthesia for surgery

What are the possible side effects of ALOXI?

The most common side effects of ALOXI are headache and constipation. Diarrhea and dizziness have also been observed.

These are not all the side effects from ALOXI. For more information ask your doctor or pharmacist.

General information about ALOXI

Medicines are sometimes prescribed for conditions other than those listed in patient information leaflets. ALOXI was prescribed for your medical condition.

This leaflet summarizes the most important information about ALOXI. If you would like more information, talk with your doctor. You can ask your doctor or pharmacist for information about ALOXI that is written for health professionals. You can also visit the ALOXI web site at www.ALOXI.com.

What are the ingredients in ALOXI?

Active ingredient: palonosetron hydrochloride

Inactive ingredients: mannitol, disodium edetate, and citrate buffer in water

Rx Only

Mfd by Catalent Pharma Solutions, Albuquerque, NM, USA or Pierre Fabre, Médicament Production, Idron, Aquitaine, France and Helsinn Birex Pharmaceuticals, Dublin, Ireland

HELSINN, Mfd for Helsinn Healthcare SA, Switzerland

MGI PHARMA, INC. Distributed and marketed by MGI PHARMA, INC. Bloomington, MN. 55437 under license of Helsinn Healthcare SA, Switzerland.

ALOXI® is a registered trademark of Helsinn Healthcare, SA, Lugano, Switzerland

©2008 MGI PHARMA, INC. Bloomington, MN 55437 U.S.A. 445091002

2/08